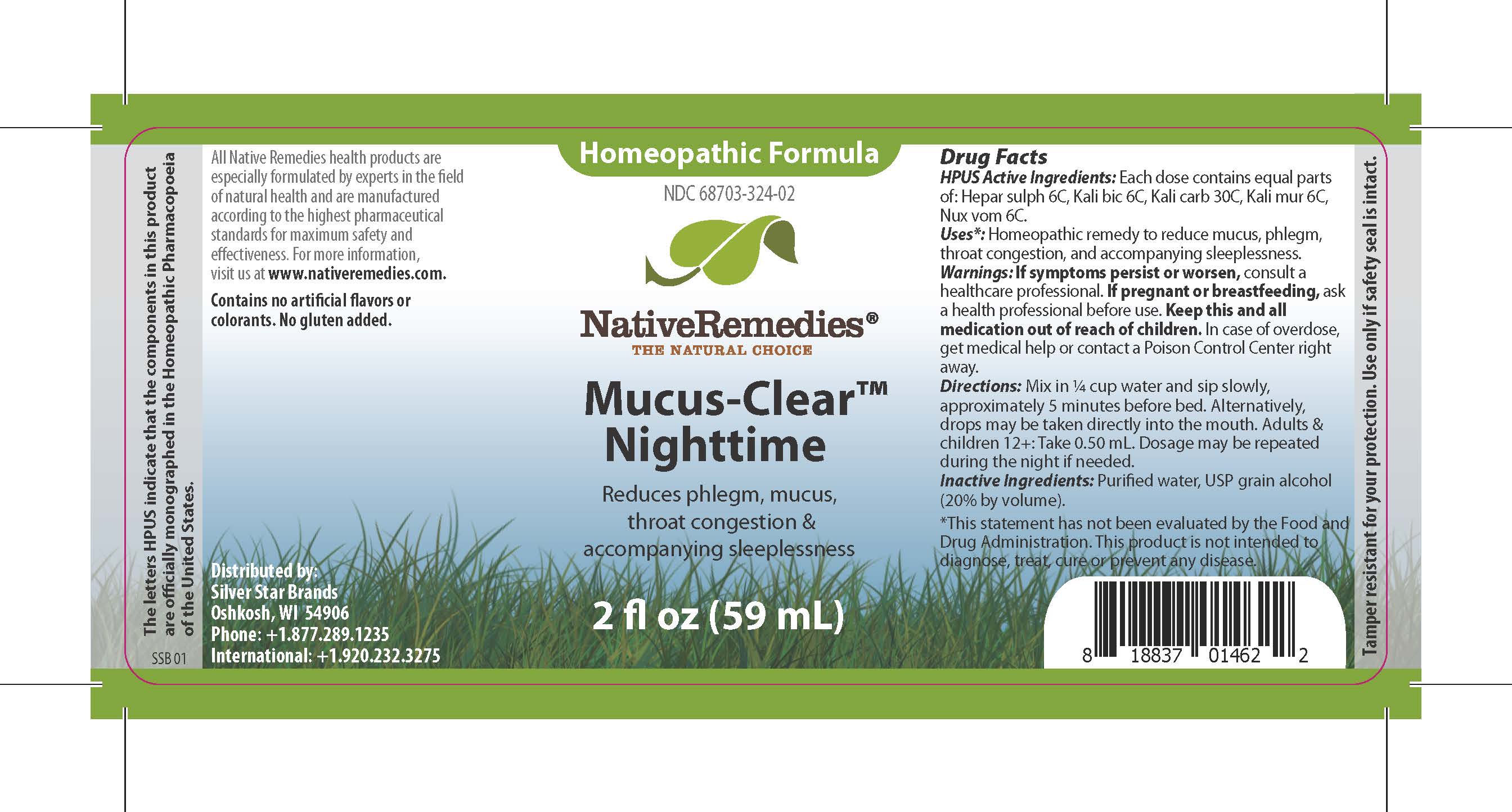 DRUG LABEL: Mucus-Clear Nighttime
NDC: 68703-324 | Form: LIQUID
Manufacturer: Silver Star Brands
Category: homeopathic | Type: HUMAN OTC DRUG LABEL
Date: 20250101

ACTIVE INGREDIENTS: POTASSIUM CHLORIDE 6 [hp_C]/59 mL; POTASSIUM CARBONATE 30 [hp_C]/59 mL; POTASSIUM DICHROMATE 6 [hp_C]/59 mL; STRYCHNOS NUX-VOMICA SEED 6 [hp_C]/59 mL; CALCIUM SULFIDE 6 [hp_C]/59 mL
INACTIVE INGREDIENTS: ALCOHOL; WATER

NativeRemedies® Mucus-Clear™ Nighttime

HPUS Active Ingredient: Each dose contains equal parts of: Hepar sulph 6C, Kali bic 6C, Kali carb 30C, Kali mur 6C, Nux vom 6C.

The letters HPUS indicate that the components in this product are officially monographed in the Homeopathic Pharmacopoeia of the United States.

Uses*:

Uses*: Homeopathic remedy to reduce mucus, phlegm, throat congestion, and accompanying sleeplessness.

*This statement has not been evaluated by the Food and Drug Administration. This product is not intended to diagnose, treat, cure or prevent any disease.

Warnings

Warnings: If symptoms persist or worsen, consult a healthcare professional. If pregnant or breastfeeding, ask a health professional before use. Keep this and all medication out of reach of children. In case of overdose, get medical help or contact a Poison Control Center right away.

Directions

Directions: Mix in 1/4 cup water and sip slowly, approximately 5 minutes before bed. Alternatively, drops may be taken directly into the mouth. Adults & children 12+: Take 0.50 mL. Dosage may be repeated during the night if needed.

OTHER SAFETY INFORMATION

Contains no artificial flavors or colorants. No gluten added.

Tamper resistant for your protection. Use only if safety seal is intact.

Inactive Ingredients

Inactive Ingredients: Purified water, USP grain alcohol (20% by volume).

KEEP OUT OF REACH OF CHILDREN

Keep this and all medication out of reach of children.

PREGNANCY OR BREAST FEEDING

If pregnant or breastfeeding, ask a healthprofessional before use.

PURPOSE

Reduces phlegm, mucus, throat congestion & accompanying sleeplessness.